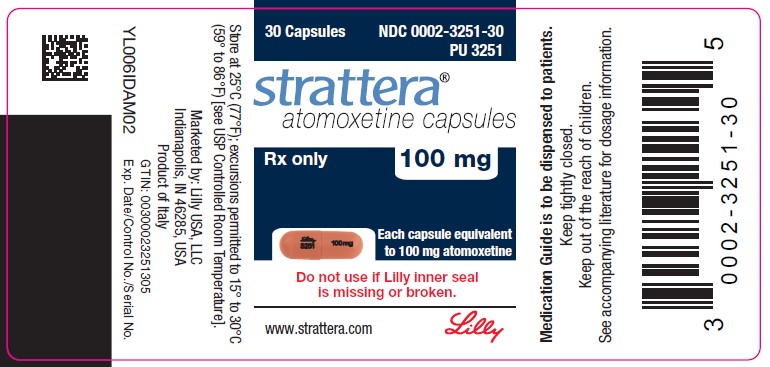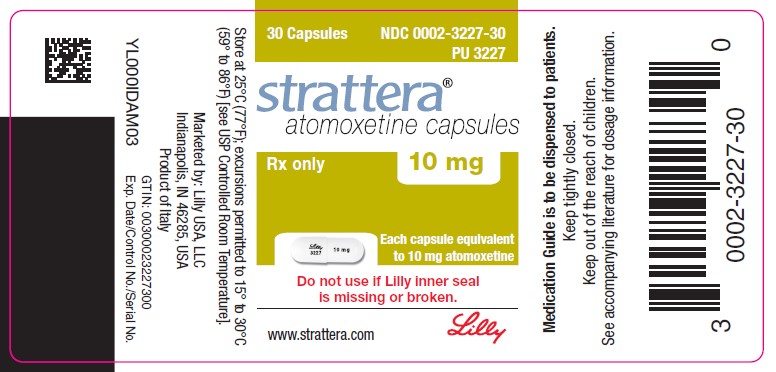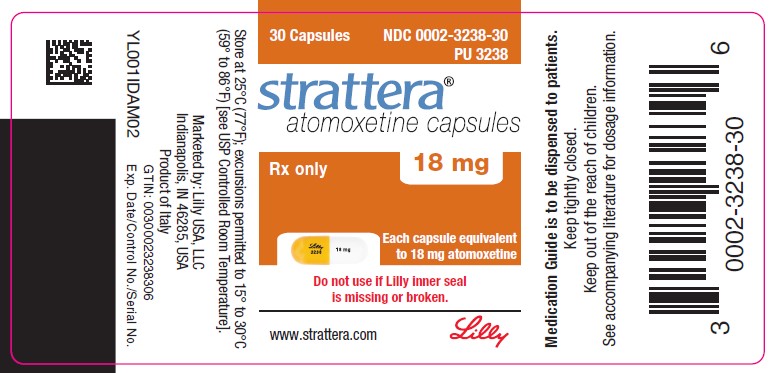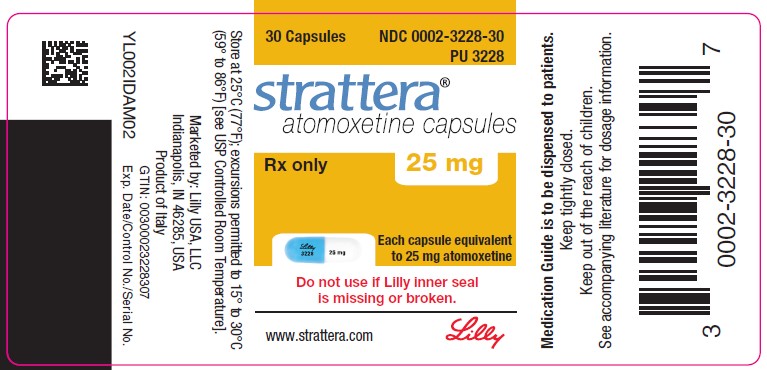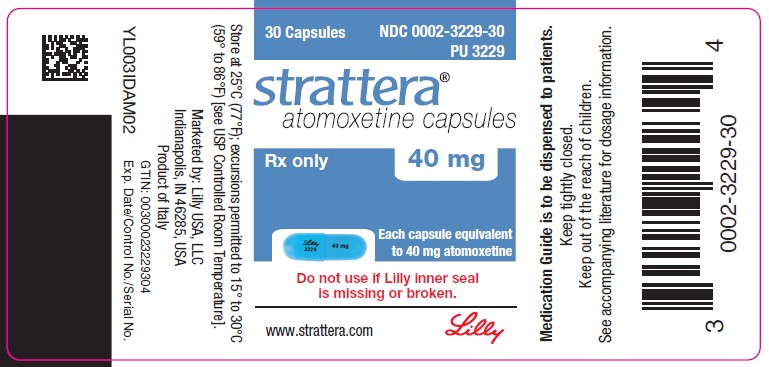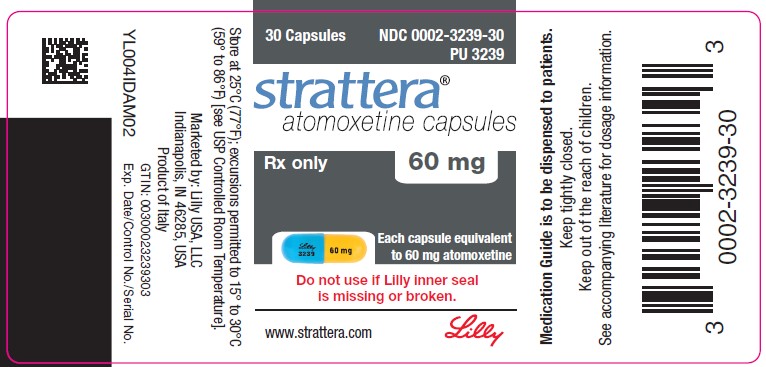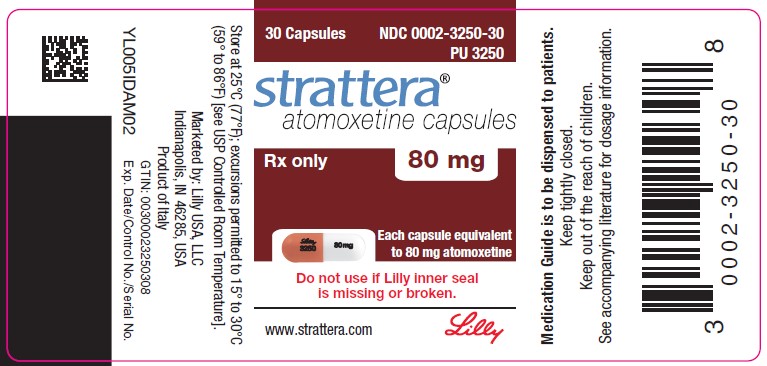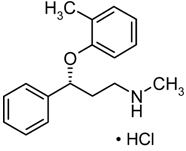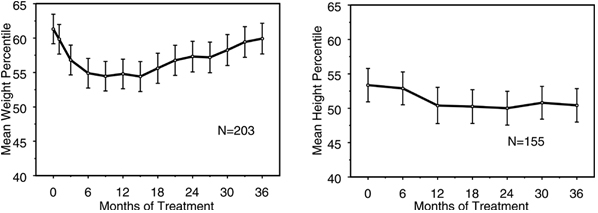 DRUG LABEL: Strattera
NDC: 0002-3227 | Form: CAPSULE
Manufacturer: Eli Lilly and Company

Category: prescription | Type: HUMAN PRESCRIPTION DRUG LABEL
Date: 20251231

ACTIVE INGREDIENTS: Atomoxetine hydrochloride 10 mg/1 1
INACTIVE INGREDIENTS: Starch, Corn; Dimethicone, Unspecified; Gelatin, Unspecified; Sodium Lauryl Sulfate; Titanium Dioxide

HIGHLIGHTS OF PRESCRIBING INFORMATION

These highlights do not include all the information needed to use STRATTERA safely and effectively. See full prescribing information for STRATTERA.
STRATTERA® (atomoxetine) capsules, for oral use
Initial U.S. Approval: 2002

RECENT MAJOR CHANGES

Dosage and Administration, Screen for Bipolar Disorder Prior to Starting STRATTERA (2.4) | 1/2022
Warnings and Precautions, Emergence of New Psychotic or Manic Symptoms (5.5) | 1/2022
Warnings and Precautions, Screening Patients for Bipolar Disorder (5.6) | 1/2022
Warnings and Precautions, Aggressive Behavior or Hostility (5.7) | 1/2022

WARNING: SUICIDAL IDEATION IN CHILDREN AND ADOLESCENTS

See full prescribing information for complete boxed warning.

- Increased risk of suicidal ideation in children or adolescents (5.1)
- No suicides occurred in clinical trials (5.1)
- Patients started on therapy should be monitored closely (5.1)

1 INDICATIONS AND USAGE

STRATTERA® is a selective norepinephrine reuptake inhibitor indicated for the treatment of Attention-Deficit/Hyperactivity Disorder (ADHD). (1.1)

2 DOSAGE AND ADMINISTRATION

Initial, Target and Maximum Daily Dose (2.1)

(Acute and Maintenance/Extended Treatment)

Body Weight | Initial Daily Dose | Target Total Daily Dose | Maximum Total Daily Dose
Children and adolescents up to 70 kg | 0.5 mg/kg | 1.2 mg/kg | 1.4 mg/kg
Children and adolescents over 70 kg and adults | 40 mg | 80 mg | 100 mg

Dosing adjustment — Hepatic Impairment, Strong CYP2D6 Inhibitor, and in patients known to be CYP2D6 poor metabolizers (PMs). (2.5, 12.3)

3 DOSAGE FORMS AND STRENGTHS

Each capsule contains atomoxetine HCl equivalent to 10, 18, 25, 40, 60, 80, or 100 mg of atomoxetine. (3, 11, 16)

4 CONTRAINDICATIONS

- Hypersensitivity to atomoxetine or other constituents of product. (4.1)
- STRATTERA use within 2 weeks after discontinuing MAOI or other drugs that affect brain monoamine concentrations. (4.2, 7.1)
- Narrow Angle Glaucoma. (4.3)
- Pheochromocytoma or history of pheochromocytoma. (4.4)
- Severe Cardiovascular Disorders that might deteriorate with clinically important increases in HR and BP. (4.5)

5 WARNINGS AND PRECAUTIONS

- Suicidal Ideation – Monitor for suicidality, clinical worsening, and unusual changes in behavior. (5.1)
- Severe Liver Injury – Should be discontinued and not restarted in patients with jaundice or laboratory evidence of liver injury. (5.2)
- Serious Cardiovascular Events – Sudden death, stroke and myocardial infarction have been reported in association with atomoxetine treatment. Patients should have a careful history and physical exam to assess for presence of cardiovascular disease. STRATTERA generally should not be used in children or adolescents with known serious structural cardiac abnormalities, cardiomyopathy, serious heart rhythm abnormalities, or other serious cardiac problems that may place them at increased vulnerability to its noradrenergic effects. Consideration should be given to not using STRATTERA in adults with clinically significant cardiac abnormalities. (5.3)
- Emergent Cardiovascular Symptoms – Patients should undergo prompt cardiac evaluation. (5.3)
- Effects on Blood Pressure and Heart Rate – Increase in blood pressure and heart rate; orthostasis and syncope may occur. Use with caution in patients with hypertension, tachycardia, or cardiovascular or cerebrovascular disease. (5.4)
- Psychotic or Manic Symptoms – Consider discontinuing STRATTERA if such new symptoms occur. (5.5)
- Bipolar Disorder – Screen patients for bipolar disorder. (5.6)
- Aggressive behavior or hostility – Monitor for the appearance or worsening of aggressive behavior or hostility. (5.7)
- Possible allergic reactions, including anaphylactic reactions, angioneurotic edema, urticaria, and rash. (5.8)
- Effects on Urine Outflow – Urinary hesitancy and retention may occur. (5.9)
- Priapism – Prompt medical attention is required in the event of suspected priapism. (5.10, 17)
- Growth – Height and weight should be monitored in pediatric patients. (5.11)
- Concomitant Use of Potent CYP2D6 Inhibitors or Use in patients known to be CYP2D6 PMs – Dose adjustment of STRATTERA may be necessary. (5.13)

6 ADVERSE REACTIONS

Most common adverse reactions (≥5% and at least twice the incidence of placebo patients)

- Child and Adolescent Clinical Trials – Nausea, vomiting, fatigue, decreased appetite, abdominal pain, and somnolence. (6.1)
- Adult Clinical Trials – Constipation, dry mouth, nausea, decreased appetite, dizziness, erectile dysfunction, and urinary hesitation. (6.1)

To report SUSPECTED ADVERSE REACTIONS, contact Eli Lilly and Company at 1-800-LillyRx (1-800-545-5979) or FDA at 1-800-FDA-1088 or www.fda.gov/medwatch.

7 DRUG INTERACTIONS

- Monoamine Oxidase Inhibitors. (4.2, 7.1)
- CYP2D6 Inhibitors - Concomitant use may increase atomoxetine steady-state plasma concentrations in EMs. (7.2)
- Antihypertensive Drugs and Pressor Agents - Possible effects on blood pressure. (7.3)
- Albuterol (or other beta2 agonists) - Action of albuterol on cardiovascular system can be potentiated. (7.4)

8 USE IN SPECIFIC POPULATIONS

- Hepatic Insufficiency - Increased exposure (AUC) to atomoxetine than with normal subjects in EM subjects with moderate (Child-Pugh Class B) (2-fold increase) and severe (Child-Pugh Class C) (4-fold increase). (8.6)
- Renal Insufficiency - Higher systemic exposure to atomoxetine than healthy subjects for EM subjects with end stage renal disease - no difference when exposure corrected for mg/kg dose. (8.7)
- Patients with Concomitant Illness - Does not worsen tics in patients with ADHD and comorbid Tourette's Disorder. (8.10)
- Patients with Concomitant Illness – Does not worsen anxiety in patients with ADHD and comorbid Anxiety Disorders. (8.10)

FULL PRESCRIBING INFORMATION

WARNING: SUICIDAL IDEATION IN CHILDREN AND ADOLESCENTS

STRATTERA (atomoxetine) increased the risk of suicidal ideation in short-term studies in children or adolescents with Attention-Deficit/Hyperactivity Disorder (ADHD). Anyone considering the use of STRATTERA in a child or adolescent must balance this risk with the clinical need. Co-morbidities occurring with ADHD may be associated with an increase in the risk of suicidal ideation and/or behavior. Patients who are started on therapy should be monitored closely for suicidality (suicidal thinking and behavior), clinical worsening, or unusual changes in behavior. Families and caregivers should be advised of the need for close observation and communication with the prescriber. STRATTERA is approved for ADHD in pediatric and adult patients. STRATTERA is not approved for major depressive disorder.

Pooled analyses of short-term (6 to 18 weeks) placebo-controlled trials of STRATTERA in children and adolescents (a total of 12 trials involving over 2200 patients, including 11 trials in ADHD and 1 trial in enuresis) have revealed a greater risk of suicidal ideation early during treatment in those receiving STRATTERA compared to placebo. The average risk of suicidal ideation in patients receiving STRATTERA was 0.4% (5/1357 patients), compared to none in placebo-treated patients (851 patients). No suicides occurred in these trials [see Warnings and Precautions (5.1)].

1 INDICATIONS AND USAGE

1.1 Attention-Deficit/Hyperactivity Disorder (ADHD)

STRATTERA is indicated for the treatment of Attention-Deficit/Hyperactivity Disorder (ADHD).

The efficacy of STRATTERA Capsules was established in seven clinical trials in outpatients with ADHD: four 6 to 9-week trials in pediatric patients (ages 6 to 18), two 10-week trial in adults, and one maintenance trial in pediatrics (ages 6 to 15) [see Clinical Studies (14)].

1.2 Diagnostic Considerations

A diagnosis of ADHD (DSM-IV) implies the presence of hyperactive-impulsive or inattentive symptoms that cause impairment and that were present before age 7 years. The symptoms must be persistent, must be more severe than is typically observed in individuals at a comparable level of development, must cause clinically significant impairment, e.g., in social, academic, or occupational functioning, and must be present in 2 or more settings, e.g., school (or work) and at home. The symptoms must not be better accounted for by another mental disorder.

The specific etiology of ADHD is unknown, and there is no single diagnostic test. Adequate diagnosis requires the use not only of medical but also of special psychological, educational, and social resources. Learning may or may not be impaired. The diagnosis must be based upon a complete history and evaluation of the patient and not solely on the presence of the required number of DSM-IV characteristics.

For the Inattentive Type, at least 6 of the following symptoms must have persisted for at least 6 months: lack of attention to details/careless mistakes, lack of sustained attention, poor listener, failure to follow through on tasks, poor organization, avoids tasks requiring sustained mental effort, loses things, easily distracted, forgetful. For the Hyperactive-Impulsive Type, at least 6 of the following symptoms must have persisted for at least 6 months: fidgeting/squirming, leaving seat, inappropriate running/climbing, difficulty with quiet activities, “on the go,” excessive talking, blurting answers, can't wait turn, intrusive. For a Combined Type diagnosis, both inattentive and hyperactive-impulsive criteria must be met.

1.3 Need for Comprehensive Treatment Program

STRATTERA is indicated as an integral part of a total treatment program for ADHD that may include other measures (psychological, educational, social) for patients with this syndrome. Drug treatment may not be indicated for all patients with this syndrome. Drug treatment is not intended for use in the patient who exhibits symptoms secondary to environmental factors and/or other primary psychiatric disorders, including psychosis. Appropriate educational placement is essential in children and adolescents with this diagnosis and psychosocial intervention is often helpful. When remedial measures alone are insufficient, the decision to prescribe drug treatment medication will depend upon the physician's assessment of the chronicity and severity of the patient's symptoms.

2 DOSAGE AND ADMINISTRATION

2.1 Acute Treatment

Dosing of children and adolescents up to 70 kg body weight — STRATTERA should be initiated at a total daily dose of approximately 0.5 mg/kg and increased after a minimum of 3 days to a target total daily dose of approximately 1.2 mg/kg administered either as a single daily dose in the morning or as evenly divided doses in the morning and late afternoon/early evening. No additional benefit has been demonstrated for doses higher than 1.2 mg/kg/day [see Clinical Studies (14)].

The total daily dose in children and adolescents should not exceed 1.4 mg/kg or 100 mg, whichever is less.

Dosing of children and adolescents over 70 kg body weight and adults — STRATTERA should be initiated at a total daily dose of 40 mg and increased after a minimum of 3 days to a target total daily dose of approximately 80 mg administered either as a single daily dose in the morning or as evenly divided doses in the morning and late afternoon/early evening. After 2 to 4 additional weeks, the dose may be increased to a maximum of 100 mg in patients who have not achieved an optimal response. There are no data that support increased effectiveness at higher doses [see Clinical Studies (14)].

The maximum recommended total daily dose in children and adolescents over 70 kg and adults is 100 mg.

2.2 Maintenance/Extended Treatment

It is generally agreed that pharmacological treatment of ADHD may be needed for extended periods. The benefit of maintaining pediatric patients (ages 6-15 years) with ADHD on STRATTERA after achieving a response in a dose range of 1.2 to 1.8 mg/kg/day was demonstrated in a controlled trial. Patients assigned to STRATTERA in the maintenance phase were generally continued on the same dose used to achieve a response in the open label phase. The physician who elects to use STRATTERA for extended periods should periodically reevaluate the long-term usefulness of the drug for the individual patient [see Clinical Studies (14.1)].

2.3 General Dosing Information

STRATTERA may be taken with or without food.

STRATTERA can be discontinued without being tapered.

STRATTERA capsules are not intended to be opened, they should be taken whole [see Patient Counseling Information (17)].

The safety of single doses over 120 mg and total daily doses above 150 mg have not been systematically evaluated.

2.4 Screen for Bipolar Disorder Prior to Starting STRATTERA

Prior to initiating treatment with STRATTERA, screen patients for a personal or family history of bipolar disorder, mania, or hypomania [see Warnings and Precautions (5.6)].

2.5 Dosing in Specific Populations

Dosing adjustment for hepatically impaired patients — For those ADHD patients who have hepatic insufficiency (HI), dosage adjustment is recommended as follows: For patients with moderate HI (Child-Pugh Class B), initial and target doses should be reduced to 50% of the normal dose (for patients without HI). For patients with severe HI (Child-Pugh Class C), initial dose and target doses should be reduced to 25% of normal [see Use in Specific Populations (8.6)].

Dosing adjustment for use with a strong CYP2D6 inhibitor or in patients who are known to be CYP2D6 PMs — In children and adolescents up to 70 kg body weight administered strong CYP2D6 inhibitors, e.g., paroxetine, fluoxetine, and quinidine, or in patients who are known to be CYP2D6 PMs, STRATTERA should be initiated at 0.5 mg/kg/day and only increased to the usual target dose of 1.2 mg/kg/day if symptoms fail to improve after 4 weeks and the initial dose is well tolerated.

In children and adolescents over 70 kg body weight and adults administered strong CYP2D6 inhibitors, e.g., paroxetine, fluoxetine, and quinidine, STRATTERA should be initiated at 40 mg/day and only increased to the usual target dose of 80 mg/day if symptoms fail to improve after 4 weeks and the initial dose is well tolerated.

3 DOSAGE FORMS AND STRENGTHS

Each capsule contains atomoxetine HCl equivalent to 10 mg (Opaque White, Opaque White), 18 mg (Gold, Opaque White), 25 mg (Opaque Blue, Opaque White), 40 mg (Opaque Blue, Opaque Blue), 60 mg (Opaque Blue, Gold), 80 mg (Opaque Brown, Opaque White), or 100 mg (Opaque Brown, Opaque Brown) of atomoxetine.

4 CONTRAINDICATIONS

4.1 Hypersensitivity

STRATTERA is contraindicated in patients known to be hypersensitive to atomoxetine or other constituents of the product [see Warnings and Precautions (5.8)].

4.2 Monoamine Oxidase Inhibitors (MAOI)

STRATTERA should not be taken with an MAOI, or within 2 weeks after discontinuing an MAOI. Treatment with an MAOI should not be initiated within 2 weeks after discontinuing STRATTERA. With other drugs that affect brain monoamine concentrations, there have been reports of serious, sometimes fatal reactions (including hyperthermia, rigidity, myoclonus, autonomic instability with possible rapid fluctuations of vital signs, and mental status changes that include extreme agitation progressing to delirium and coma) when taken in combination with an MAOI. Some cases presented with features resembling neuroleptic malignant syndrome. Such reactions may occur when these drugs are given concurrently or in close proximity [see Drug Interactions (7.1)].

4.3 Narrow Angle Glaucoma

In clinical trials, STRATTERA use was associated with an increased risk of mydriasis and therefore its use is not recommended in patients with narrow angle glaucoma.

4.4 Pheochromocytoma

Serious reactions, including elevated blood pressure and tachyarrhythmia, have been reported in patients with pheochromocytoma or a history of pheochromocytoma who received STRATTERA. Therefore, STRATTERA should not be taken by patients with pheochromocytoma or a history of pheochromocytoma.

4.5 Severe Cardiovascular Disorders

STRATTERA should not be used in patients with severe cardiac or vascular disorders whose condition would be expected to deteriorate if they experience increases in blood pressure or heart rate that could be clinically important (for example, 15 to 20 mm Hg in blood pressure or 20 beats per minute in heart rate) [see Warnings and Precautions (5.4)].

5 WARNINGS AND PRECAUTIONS

5.1 Suicidal Ideation

STRATTERA increased the risk of suicidal ideation in short-term studies in children and adolescents with Attention-Deficit/Hyperactivity Disorder (ADHD). Pooled analyses of short-term (6 to 18 weeks) placebo-controlled trials of STRATTERA in children and adolescents have revealed a greater risk of suicidal ideation early during treatment in those receiving STRATTERA. There were a total of 12 trials (11 in ADHD and 1 in enuresis) involving over 2200 patients (including 1357 patients receiving STRATTERA and 851 receiving placebo). The average risk of suicidal ideation in patients receiving STRATTERA was 0.4% (5/1357 patients), compared to none in placebo-treated patients. There was 1 suicide attempt among these approximately 2200 patients, occurring in a patient treated with STRATTERA. No suicides occurred in these trials. All reactions occurred in children 12 years of age or younger. All reactions occurred during the first month of treatment. It is unknown whether the risk of suicidal ideation in pediatric patients extends to longer-term use. A similar analysis in adult patients treated with STRATTERA for either ADHD or major depressive disorder (MDD) did not reveal an increased risk of suicidal ideation or behavior in association with the use of STRATTERA.

All pediatric patients being treated with STRATTERA should be monitored appropriately and observed closely for clinical worsening, suicidality, and unusual changes in behavior, especially during the initial few months of a course of drug therapy, or at times of dose changes, either increases or decreases.

The following symptoms have been reported with STRATTERA: anxiety, agitation, panic attacks, insomnia, irritability, hostility, aggressiveness, impulsivity, akathisia (psychomotor restlessness), hypomania and mania. Although a causal link between the emergence of such symptoms and the emergence of suicidal impulses has not been established, there is a concern that such symptoms may represent precursors to emerging suicidality. Thus, patients being treated with STRATTERA should be observed for the emergence of such symptoms.

Consideration should be given to changing the therapeutic regimen, including possibly discontinuing the medication, in patients who are experiencing emergent suicidality or symptoms that might be precursors to emerging suicidality, especially if these symptoms are severe or abrupt in onset, or were not part of the patient's presenting symptoms.

Families and caregivers of pediatric patients being treated with STRATTERA should be alerted about the need to monitor patients for the emergence of agitation, irritability, unusual changes in behavior, and the other symptoms described above, as well as the emergence of suicidality, and to report such symptoms immediately to healthcare providers. Such monitoring should include daily observation by families and caregivers.

5.2 Severe Liver Injury

Postmarketing reports indicate that STRATTERA can cause severe liver injury. Although no evidence of liver injury was detected in clinical trials of about 6000 patients, there have been rare cases of clinically significant liver injury that were considered probably or possibly related to STRATTERA use in postmarketing experience. Rare cases of liver failure have also been reported, including a case that resulted in a liver transplant. Because of probable underreporting, it is impossible to provide an accurate estimate of the true incidence of these reactions. Reported cases of liver injury occurred within 120 days of initiation of atomoxetine in the majority of cases and some patients presented with markedly elevated liver enzymes [>20 X upper limit of normal (ULN)], and jaundice with significantly elevated bilirubin levels (>2 X ULN), followed by recovery upon atomoxetine discontinuation. In one patient, liver injury, manifested by elevated hepatic enzymes up to 40 X ULN and jaundice with bilirubin up to 12 X ULN, recurred upon rechallenge, and was followed by recovery upon drug discontinuation, providing evidence that STRATTERA likely caused the liver injury. Such reactions may occur several months after therapy is started, but laboratory abnormalities may continue to worsen for several weeks after drug is stopped. The patient described above recovered from his liver injury, and did not require a liver transplant.

STRATTERA should be discontinued in patients with jaundice or laboratory evidence of liver injury, and should not be restarted. Laboratory testing to determine liver enzyme levels should be done upon the first symptom or sign of liver dysfunction (e.g., pruritus, dark urine, jaundice, right upper quadrant tenderness, or unexplained “flu like” symptoms) [see Warnings and Precautions (5.12); Patient Counseling Information (17)].

5.3 Serious Cardiovascular Events

Sudden Death and Pre-existing Structural Cardiac Abnormalities or Other Serious Heart Problems

Children and Adolescents — Sudden death has been reported in association with atomoxetine treatment at usual doses in children and adolescents with structural cardiac abnormalities or other serious heart problems. Although some serious heart problems alone carry an increased risk of sudden death, atomoxetine generally should not be used in children or adolescents with known serious structural cardiac abnormalities, cardiomyopathy, serious heart rhythm abnormalities, or other serious cardiac problems that may place them at increased vulnerability to the noradrenergic effects of atomoxetine.

Adults — Sudden deaths, stroke, and myocardial infarction have been reported in adults taking atomoxetine at usual doses for ADHD. Although the role of atomoxetine in these adult cases is also unknown, adults have a greater likelihood than children of having serious structural cardiac abnormalities, cardiomyopathy, serious heart rhythm abnormalities, coronary artery disease, or other serious cardiac problems. Consideration should be given to not treating adults with clinically significant cardiac abnormalities.

Assessing Cardiovascular Status in Patients being Treated with Atomoxetine

Children, adolescents, or adults who are being considered for treatment with atomoxetine should have a careful history (including assessment for a family history of sudden death or ventricular arrhythmia) and physical exam to assess for the presence of cardiac disease, and should receive further cardiac evaluation if findings suggest such disease (e.g., electrocardiogram and echocardiogram). Patients who develop symptoms such as exertional chest pain, unexplained syncope, or other symptoms suggestive of cardiac disease during atomoxetine treatment should undergo a prompt cardiac evaluation.

5.4 Effects on Blood Pressure and Heart Rate

STRATTERA should be used with caution in patients whose underlying medical conditions could be worsened by increases in blood pressure or heart rate such as certain patients with hypertension, tachycardia, or cardiovascular or cerebrovascular disease. It should not be used in patients with severe cardiac or vascular disorders whose condition would be expected to deteriorate if they experienced clinically important increases in blood pressure or heart rate [see Contraindications (4.5)]. Pulse and blood pressure should be measured at baseline, following STRATTERA dose increases, and periodically while on therapy to detect possible clinically important increases.

The following table provides short-term, placebo-controlled clinical trial data for the proportions of patients having an increase in: diastolic blood pressure ≥15 mm Hg; systolic blood pressure ≥20 mm Hg; heart rate greater than or equal to 20 bpm, in both the pediatric and adult populations (see Table 1).

Table 1a
 | Pediatric Acute Placebo-Controlled |  |  |  | Adult Acute Placebo-Controlled
 | Maximumb |  | Endpoint |  | Maximumb |  | Endpoint
 | Atomoxetine | Placebo | Atomoxetine | Placebo | Atomoxetine | Placebo | Atomoxetine | Placebo
 | % | % | % | % | % | % | % | %
DBP (≥15 mm Hg) | 21.5 | 14.1 | 9.3 | 4.8 | 12.6 | 8.7 | 4.8 | 3.5
SBP (≥20 mm Hg) | 12.5 | 8.7 | 4.9 | 3.3 | 12.4 | 7.8 | 4.2 | 3.2
HR (≥20 bpm) | 23.4 | 11.5 | 12.2 | 3.8 | 22.4 | 8.3 | 10.2 | 2.0
a Abbreviations: bpm=beats per minute; DBP=diastolic blood pressure; HR=heart rate; mm Hg=millimeters mercury; SBP=systolic blood pressure.
b Proportion of patients meeting threshold at any one time during clinical trial.

In placebo-controlled registration studies involving pediatric patients, tachycardia was identified as an adverse event for 0.3% (5/1597) of these STRATTERA patients compared with 0% (0/934) of placebo patients. The mean heart rate increase in extensive metabolizer (EM) patients was 5.0 beats/minute, and in poor metabolizer (PM) patients 9.4 beats/minute.

In adult clinical trials where EM/PM status was available, the mean heart rate increase in PM patients was significantly higher than in EM patients (11 beats/minute versus 7.5 beats/minute). The heart rate effects could be clinically important in some PM patients.

In placebo-controlled registration studies involving adult patients, tachycardia was identified as an adverse event for 1.5% (8/540) of STRATTERA patients compared with 0.5% (2/402) of placebo patients.

In adult clinical trials where EM/PM status was available, the mean change from baseline in diastolic blood pressure in PM patients was higher than in EM patients (4.21 versus 2.13 mm Hg) as was the mean change from baseline in systolic blood pressure (PM: 2.75 versus EM: 2.40 mm Hg). The blood pressure effects could be clinically important in some PM patients.

Orthostatic hypotension and syncope have been reported in patients taking STRATTERA. In child and adolescent registration studies, 0.2% (12/5596) of STRATTERA-treated patients experienced orthostatic hypotension and 0.8% (46/5596) experienced syncope. In short-term child and adolescent registration studies, 1.8% (6/340) of STRATTERA-treated patients experienced orthostatic hypotension compared with 0.5% (1/207) of placebo-treated patients. Syncope was not reported during short-term child and adolescent placebo-controlled ADHD registration studies. STRATTERA should be used with caution in any condition that may predispose patients to hypotension, or conditions associated with abrupt heart rate or blood pressure changes.

5.5 Emergence of New Psychotic or Manic Symptoms

Psychotic or manic symptoms (e.g., hallucinations, delusional thinking, or mania) in patients without a prior history of psychotic illness or mania can be caused by STRATTERA at usual doses. If such symptoms occur, consider discontinuing STRATTERA.

5.6 Screening Patients for Bipolar Disorder

Patients with bipolar disorder or risk factors for bipolar disorder may be at increased risk of developing mania or mixed episodes during treatment with STRATTERA. It may not be possible to determine whether a manic or mixed episode that appears during treatment with STRATTERA is due to an adverse reaction to STRATTERA or a patient’s underlying bipolar disorder. Before initiating treatment with STRATTERA, patients should be adequately screened for risk factors for bipolar disorder such as a personal or family history of mania and depression.

5.7 Aggressive Behavior or Hostility

Patients beginning treatment with STRATTERA should be monitored for the appearance or worsening of aggressive behavior or hostility. There is evidence that STRATTERA may cause the emergence or worsening of aggressive behavior or hostility. ADHD and other mental illnesses can be associated with irritability, which can make it difficult to determine if the drug or the underlying psychiatric condition is causing the emergence or worsening of aggressive behavior or hostility in specific patients. If such symptoms occur during treatment, consider a possible causal role of STRATTERA.

5.8 Allergic Events

Although uncommon, allergic reactions, including anaphylactic reactions, angioneurotic edema, urticaria, and rash, have been reported in patients taking STRATTERA.

5.9 Effects on Urine Outflow from the Bladder

In adult ADHD controlled trials, the rates of urinary retention (1.7%, 9/540) and urinary hesitation (5.6%, 30/540) were increased among atomoxetine subjects compared with placebo subjects (0%, 0/402; 0.5%, 2/402, respectively). Two adult atomoxetine subjects and no placebo subjects discontinued from controlled clinical trials because of urinary retention. A complaint of urinary retention or urinary hesitancy should be considered potentially related to atomoxetine.

5.10 Priapism

Rare postmarketing cases of priapism, defined as painful and nonpainful penile erection lasting more than 4 hours, have been reported for pediatric and adult patients treated with STRATTERA. The erections resolved in cases in which follow-up information was available, some following discontinuation of STRATTERA. Prompt medical attention is required in the event of suspected priapism.

5.11 Effects on Growth

Data on the long-term effects of STRATTERA on growth come from open-label studies, and weight and height changes are compared to normative population data. In general, the weight and height gain of pediatric patients treated with STRATTERA lags behind that predicted by normative population data for about the first 9-12 months of treatment. Subsequently, weight gain rebounds and at about 3 years of treatment, patients treated with STRATTERA have gained 17.9 kg on average, 0.5 kg more than predicted by their baseline data. After about 12 months, gain in height stabilizes, and at 3 years, patients treated with STRATTERA have gained 19.4 cm on average, 0.4 cm less than predicted by their baseline data (see Figure 1 below).

Figure 1: Mean Weight and Height Percentiles Over Time for Patients with Three Years of STRATTERA Treatment

This growth pattern was generally similar regardless of pubertal status at the time of treatment initiation. Patients who were pre-pubertal at the start of treatment (girls ≤8 years old, boys ≤9 years old) gained an average of 2.1 kg and 1.2 cm less than predicted after three years. Patients who were pubertal (girls >8 to ≤13 years old, boys >9 to ≤14 years old) or late pubertal (girls >13 years old, boys >14 years old) had average weight and height gains that were close to or exceeded those predicted after three years of treatment.

Growth followed a similar pattern in both extensive and poor metabolizers (EMs, PMs). PMs treated for at least two years gained an average of 2.4 kg and 1.1 cm less than predicted, while EMs gained an average of 0.2 kg and 0.4 cm less than predicted.

In short-term controlled studies (up to 9 weeks), STRATTERA-treated patients lost an average of 0.4 kg and gained an average of 0.9 cm, compared to a gain of 1.5 kg and 1.1 cm in the placebo-treated patients. In a fixed-dose controlled trial, 1.3%, 7.1%, 19.3%, and 29.1% of patients lost at least 3.5% of their body weight in the placebo, 0.5, 1.2, and 1.8 mg/kg/day dose groups.

Growth should be monitored during treatment with STRATTERA.

5.12 Laboratory Tests

Routine laboratory tests are not required.

CYP2D6 metabolism — Poor metabolizers (PMs) of CYP2D6 have a 10-fold higher AUC and a 5-fold higher peak concentration to a given dose of STRATTERA compared with extensive metabolizers (EMs). Approximately 7% of a Caucasian population are PMs. Laboratory tests are available to identify CYP2D6 PMs. The blood levels in PMs are similar to those attained by taking strong inhibitors of CYP2D6. The higher blood levels in PMs lead to a higher rate of some adverse effects of STRATTERA [see Adverse Reactions (6.1)].

5.13 Concomitant Use of Potent CYP2D6 Inhibitors or Use in Patients who are known to be CYP2D6 PMs

Atomoxetine is primarily metabolized by the CYP2D6 pathway to 4-hydroxyatomoxetine. Dosage adjustment of STRATTERA may be necessary when coadministered with potent CYP2D6 inhibitors (e.g., paroxetine, fluoxetine, and quinidine) or when administered to CYP2D6 PMs [see Dosage and Administration (2.5) and Drug Interactions (7.2)].

6 ADVERSE REACTIONS

6.1 Clinical Trials Experience

STRATTERA was administered to 5382 children or adolescent patients with ADHD and 1007 adults with ADHD in clinical studies. During the ADHD clinical trials, 1625 children and adolescent patients were treated for longer than 1 year and 2529 children and adolescent patients were treated for over 6 months.

Because clinical trials are conducted under widely varying conditions, adverse reaction rates observed in the clinical trials of a drug cannot be directly compared to rates in the clinical trials of another drug and may not reflect the rates observed in practice.

Child and Adolescent Clinical Trials

Reasons for discontinuation of treatment due to adverse reactions in child and adolescent clinical trials — In acute child and adolescent placebo-controlled trials, 3.0% (48/1613) of atomoxetine subjects and 1.4% (13/945) placebo subjects discontinued for adverse reactions. For all studies, (including open-label and long-term studies), 6.3% of extensive metabolizer (EM) patients and 11.2% of poor metabolizer (PM) patients discontinued because of an adverse reaction. Among STRATTERA-treated patients, irritability (0.3%, N=5); somnolence (0.3%, N=5); aggression (0.2%, N=4); nausea (0.2%, N=4); vomiting (0.2%, N=4); abdominal pain (0.2%, N=4); constipation (0.1%, N=2); fatigue (0.1%, N=2); feeling abnormal (0.1%, N=2); and headache (0.1%, N=2) were the reasons for discontinuation reported by more than 1 patient.

Seizures — STRATTERA has not been systematically evaluated in pediatric patients with seizure disorder as these patients were excluded from clinical studies during the product's premarket testing. In the clinical development program, seizures were reported in 0.2% (12/5073) of children whose average age was 10 years (range 6 to 16 years). In these clinical trials, the seizure risk among poor metabolizers was 0.3% (1/293) compared to 0.2% (11/4741) for extensive metabolizers.

Commonly observed adverse reactions in acute child and adolescent, placebo-controlled trials — Commonly observed adverse reactions associated with the use of STRATTERA (incidence of 2% or greater) and not observed at an equivalent incidence among placebo-treated patients (STRATTERA incidence greater than placebo) are listed in Table 2. Results were similar in the BID and the QD trial except as shown in Table 3, which shows both BID and QD results for selected adverse reactions based on statistically significant Breslow-Day tests. The most commonly observed adverse reactions in patients treated with STRATTERA (incidence of 5% or greater and at least twice the incidence in placebo patients, for either BID or QD dosing) were: nausea, vomiting, fatigue, decreased appetite, abdominal pain, and somnolence (see Tables 2 and 3).

Additional data from ADHD clinical trials (controlled and uncontrolled) has shown that approximately 5 to 10% of pediatric patients experienced potentially clinically important changes in heart rate (≥20 beats per min) or blood pressure (≥15 to 20 mm Hg) [see Contraindications (4) and Warnings and Precautions (5)].

Table 2: Common Treatment–Emergent Adverse Reactions Associated with the Use of STRATTERA in Acute (up to 18 weeks) Child and Adolescent Trials
Adverse Reactiona | Percentage of Patients Reporting Reaction
 | STRATTERA (N=1597) | Placebo (N=934)
Gastrointestinal Disorders
Abdominal painb | 18 | 10
Vomiting | 11 | 6
Nausea | 10 | 5
General Disorders and Administration Site Conditions
Fatigue | 8 | 3
Irritability | 6 | 3
Therapeutic response unexpected | 2 | 1
Investigations
Weight decreased | 3 | 0
Metabolism and Nutritional Disorders
Decreased appetite | 16 | 4
Anorexia | 3 | 1
Nervous System Disorders
Headache | 19 | 15
Somnolencec | 11 | 4
Dizziness | 5 | 2
Skin and Subcutaneous Tissue Disorders
Rash | 2 | 1
a Reactions reported by at least 2% of patients treated with atomoxetine, and greater than placebo. The following reactions did not meet this criterion but were reported by more atomoxetine-treated patients than placebo-treated patients and are possibly related to atomoxetine treatment: blood pressure increased, early morning awakening (terminal insomnia), flushing, mydriasis, sinus tachycardia, asthenia, palpitations, mood swings, constipation, and dyspepsia. The following reactions were reported by at least 2% of patients treated with atomoxetine, and equal to or less than placebo: pharyngolaryngeal pain, insomnia (insomnia includes the terms, insomnia, initial insomnia, middle insomnia). The following reaction did not meet this criterion but shows a statistically significant dose relationship: pruritus.
b Abdominal pain includes the terms: abdominal pain upper, abdominal pain, stomach discomfort, abdominal discomfort, epigastric discomfort.
c Somnolence includes the terms: sedation, somnolence.

Table 3: Common Treatment-Emergent Adverse Reactions Associated with the Use of STRATTERA in Acute (up to 18 weeks) Child and Adolescent Trials
Adverse Reaction | Percentage of Patients Reporting Reaction from BID Trials |  | Percentage of Patients Reporting Reaction from QD Trials
 | STRATTERA (N=715) | Placebo (N=434) | STRATTERA (N=882) | Placebo (N=500)
Gastrointestinal Disorders
Abdominal paina | 17 | 13 | 18 | 7
Vomiting | 11 | 8 | 11 | 4
Nausea | 7 | 6 | 13 | 4
Constipationb | 2 | 1 | 1 | 0
General Disorders
Fatigue | 6 | 4 | 9 | 2
Psychiatric Disorders
Mood swingsc | 2 | 0 | 1 | 1
a Abdominal pain includes the terms: abdominal pain upper, abdominal pain, stomach discomfort, abdominal discomfort, epigastric discomfort.
b Constipation didn't meet the statistical significance on Breslow-Day test but is included in the table because of pharmacologic plausibility.
c Mood swings didn't meet the statistical significance on Breslow-Day test at 0.05 level but p-value was <0.1 (trend).

The following adverse reactions occurred in at least 2% of child and adolescent CYP2D6 PM patients and were statistically significantly more frequent in PM patients compared with CYP2D6 EM patients: insomnia (11% of PMs, 6% of EMs); weight decreased (7% of PMs, 4% of EMs); constipation (7% of PMs, 4% of EMs); depression^1 (7% of PMs, 4% of EMs); tremor (5% of PMs, 1% of EMs); excoriation (4% of PMs, 2% of EMs); middle insomnia (3% of PMs, 1% of EMs); conjunctivitis (3% of PMs, 1% of EMs); syncope (3% of PMs, 1% of EMs); early morning awakening (2% of PMs, 1% of EMs); mydriasis (2% of PMs, 1% of EMs); sedation (4% of PMs, 2% of EMs).

^1Depression includes the following terms: depression, major depression, depressive symptoms, depressed mood, dysphoria.

Adult Clinical Trials

Reasons for discontinuation of treatment due to adverse reactions in acute adult placebo-controlled trials — In the acute adult placebo-controlled trials, 11.3% (61/541) atomoxetine subjects and 3.0% (12/405) placebo subjects discontinued for adverse reactions. Among STRATTERA-treated patients, insomnia (0.9%, N=5); nausea (0.9%, N=5); chest pain (0.6%, N=3); fatigue (0.6%, N=3); anxiety (0.4%, N=2); erectile dysfunction (0.4%, N=2); mood swings (0.4%, N=2); nervousness (0.4%, N=2); palpitations (0.4%, N=2); and urinary retention (0.4%, N=2) were the reasons for discontinuation reported by more than 1 patient.

Seizures — STRATTERA has not been systematically evaluated in adult patients with a seizure disorder as these patients were excluded from clinical studies during the product's premarket testing. In the clinical development program, seizures were reported on 0.1% (1/748) of adult patients. In these clinical trials, no poor metabolizers (0/43) reported seizures compared to 0.1% (1/705) for extensive metabolizers.

Commonly observed adverse reactions in acute adult placebo-controlled trials— Commonly observed adverse reactions associated with the use of STRATTERA (incidence of 2% or greater) and not observed at an equivalent incidence among placebo-treated patients (STRATTERA incidence greater than placebo) are listed in Table 4. The most commonly observed adverse reactions in patients treated with STRATTERA (incidence of 5% or greater and at least twice the incidence in placebo patients) were: constipation, dry mouth, nausea, decreased appetite, dizziness, erectile dysfunction, and urinary hesitation (see Table 4).

Additional data from ADHD clinical trials (controlled and uncontrolled) has shown that approximately 5 to 10% of adult patients experienced potentially clinically important changes in heart rate (≥20 beats per min) or blood pressure (≥15 to 20 mm Hg) [see Contraindications (4) and Warnings and Precautions (5)].

Table 4: Common Treatment-Emergent Adverse Reactions Associated with the Use of STRATTERA in Acute (up to 25 weeks) Adult Trials
Adverse Reactiona | Percentage of Patients Reporting Reaction
 | STRATTERA (N=1697) | Placebo (N=1560)
Cardiac Disorders
Palpitations | 3 | 1
Gastrointestinal Disorders
Dry mouth | 20 | 5
Nausea | 26 | 6
Constipation | 8 | 3
Abdominal painb | 7 | 4
Dyspepsia | 4 | 2
Vomiting | 4 | 2
General Disorders and Administration Site Conditions
Fatigue | 10 | 6
Chills | 3 | 0
Feeling jittery | 2 | 1
Irritability | 5 | 3
Thirst | 2 | 1
Investigations
Weight decreased | 2 | 1
Metabolism and Nutritional Disorders
Decreased appetite | 16 | 3
Nervous System Disorders
Dizziness | 8 | 3
Somnolencec | 8 | 5
Paraesthesia | 3 | 0
Psychiatric Disorders
Abnormal dreams | 4 | 3
Insomniad | 15 | 8
Libido decreased | 3 | 1
Sleep disorder | 3 | 1
Renal and Urinary Disorders
Urinary hesitatione | 6 | 1
Dysuria | 2 | 0
Reproductive System and Breast Disorders
Erectile dysfunctionf | 8 | 1
Dysmenorrheag | 3 | 2
Ejaculation delayedf and/or ejaculation disorderf | 4 | 1
Skin and Subcutaneous Tissue Disorders
Hyperhidrosis | 4 | 1
Vascular Disorders
Hot flush | 3 | 0
a Reactions reported by at least 2% of patients treated with atomoxetine, and greater than placebo. The following reactions did not meet this criterion but were reported by more atomoxetine-treated patients than placebo-treated patients and are possibly related to atomoxetine treatment: peripheral coldness, tachycardia, prostatitis, testicular pain, orgasm abnormal, flatulence, asthenia, feeling cold, muscle spasm, dysgeusia, agitation, restlessness, micturition urgency, pollakiuria, pruritus, urticaria, flushing, tremor, menstruation irregular, rash, and urinary retention. The following reactions were reported by at least 2% of patients treated with atomoxetine, and equal to or less than placebo: anxiety, diarrhea, back pain, headache, and oropharyngeal pain.
b Abdominal pain includes the terms: abdominal pain upper, abdominal pain, stomach discomfort, abdominal discomfort, epigastric discomfort.
c Somnolence includes the terms: sedation, somnolence.
d Insomnia includes the terms: insomnia, initial insomnia, middle insomnia, and terminal insomnia.
e Urinary hesitation includes the terms: urinary hesitation, urine flow decreased.
f Based on total number of males (STRATTERA, N=943; placebo, N=869).
g Based on total number of females (STRATTERA, N=754; placebo, N=691).

The following adverse events occurred in at least 2% of adult CYP2D6 poor metaboliser (PM) patients and were statistically significantly more frequent in PM patients compared to CYP2D6 extensive metaboliser (EM) patients: vision blurred (4% of PMs, 1% of EMs); dry mouth (35% of PMs, 17% of EMs); constipation (11% of PMs, 7% of EMs); feeling jittery (5% of PMs, 2% of EMs); decreased appetite (23% of PMs, 15% of EMs); tremor (5% of PMs, 1% of EMs); insomnia (19% of PMs, 11% of EMs); sleep disorder (7% of PMs, 3% of EMs); middle insomnia (5% of PMs, 3% of EMs); terminal insomnia (3% of PMs, 1% of EMs); urinary retention (6% of PMs, 1% of EMs); erectile dysfunction (21% of PMs, 9% of EMs); ejaculation disorder (6% of PMs, 2% of EMs); hyperhidrosis (15% of PMs, 7% of EMs); peripheral coldness (3% of PMs, 1% of EMs).

Male and female sexual dysfunction — Atomoxetine appears to impair sexual function in some patients. Changes in sexual desire, sexual performance, and sexual satisfaction are not well assessed in most clinical trials because they need special attention and because patients and physicians may be reluctant to discuss them. Accordingly, estimates of the incidence of untoward sexual experience and performance cited in product labeling are likely to underestimate the actual incidence. Table 4 above displays the incidence of sexual side effects reported by at least 2% of adult patients taking STRATTERA in placebo-controlled trials.

There are no adequate and well-controlled studies examining sexual dysfunction with STRATTERA treatment. While it is difficult to know the precise risk of sexual dysfunction associated with the use of STRATTERA, physicians should routinely inquire about such possible side effects.

6.2 Postmarketing Spontaneous Reports

The following adverse reactions have been identified during post approval use of STRATTERA. Unless otherwise specified, these adverse reactions have occurred in adults and children and adolescents. Because these reactions are reported voluntarily from a population of uncertain size, it is not always possible to reliably estimate their frequency or establish a causal relationship to drug exposure.

Cardiovascular system — QT prolongation, syncope.

Peripheral vascular effects — Raynaud's phenomenon.

General disorders and administration site conditions — Lethargy.

Musculoskeletal system — Rhabdomyolysis.

Nervous system disorders — Hypoaesthesia; paraesthesia in children and adolescents; sensory disturbances; tics.

Psychiatric disorders — Depression and depressed mood; anxiety, libido changes.

Seizures — Seizures have been reported in the postmarketing period. The postmarketing seizure cases include patients with pre-existing seizure disorders and those with identified risk factors for seizures, as well as patients with neither a history of nor identified risk factors for seizures. The exact relationship between STRATTERA and seizures is difficult to evaluate due to uncertainty about the background risk of seizures in ADHD patients.

Skin and subcutaneous tissue disorders — Alopecia, hyperhidrosis.

Urogenital system — Male pelvic pain; urinary hesitation in children and adolescents; urinary retention in children and adolescents.

7 DRUG INTERACTIONS

7.1 Monoamine Oxidase Inhibitors

With other drugs that affect brain monoamine concentrations, there have been reports of serious, sometimes fatal reactions (including hyperthermia, rigidity, myoclonus, autonomic instability with possible rapid fluctuations of vital signs, and mental status changes that include extreme agitation progressing to delirium and coma) when taken in combination with an MAOI. Some cases presented with features resembling neuroleptic malignant syndrome. Such reactions may occur when these drugs are given concurrently or in close proximity [see Contraindications (4.2)].

7.2 Effect of CYP2D6 Inhibitors on Atomoxetine

In extensive metabolizers (EMs), inhibitors of CYP2D6 (e.g., paroxetine, fluoxetine, and quinidine) increase atomoxetine steady-state plasma concentrations to exposures similar to those observed in poor metabolizers (PMs). In EM individuals treated with paroxetine or fluoxetine, the AUC of atomoxetine is approximately 6- to 8-fold and Css, max is about 3- to 4-fold greater than atomoxetine alone.

In vitro studies suggest that coadministration of cytochrome P450 inhibitors to PMs will not increase the plasma concentrations of atomoxetine.

7.3 Antihypertensive Drugs and Pressor Agents

Because of possible effects on blood pressure, STRATTERA should be used cautiously with antihypertensive drugs and pressor agents (e.g., dopamine, dobutamine) or other drugs that increase blood pressure.

7.4 Albuterol

STRATTERA should be administered with caution to patients being treated with systemically-administered (oral or intravenous) albuterol (or other beta2 agonists) because the action of albuterol on the cardiovascular system can be potentiated resulting in increases in heart rate and blood pressure. Albuterol (600 mcg iv over 2 hours) induced increases in heart rate and blood pressure. These effects were potentiated by atomoxetine (60 mg BID for 5 days) and were most marked after the initial coadministration of albuterol and atomoxetine. However, these effects on heart rate and blood pressure were not seen in another study after the coadministration with inhaled dose of albuterol (200-800 mcg) and atomoxetine (80 mg QD for 5 days) in 21 healthy Asian subjects who were excluded for poor metabolizer status.

7.5 Effect of Atomoxetine on P450 Enzymes

Atomoxetine did not cause clinically important inhibition or induction of cytochrome P450 enzymes, including CYP1A2, CYP3A, CYP2D6, and CYP2C9.

CYP3A Substrate (e.g., Midazolam) — Coadministration of STRATTERA (60 mg BID for 12 days) with midazolam, a model compound for CYP3A4 metabolized drugs (single dose of 5 mg), resulted in 15% increase in AUC of midazolam. No dose adjustment is recommended for drugs metabolized by CYP3A.

CYP2D6 Substrate (e.g., Desipramine) — Coadministration of STRATTERA (40 or 60 mg BID for 13 days) with desipramine, a model compound for CYP2D6 metabolized drugs (single dose of 50 mg), did not alter the pharmacokinetics of desipramine. No dose adjustment is recommended for drugs metabolized by CYP2D6.

7.6 Alcohol

Consumption of ethanol with STRATTERA did not change the intoxicating effects of ethanol.

7.7 Methylphenidate

Coadministration of methylphenidate with STRATTERA did not increase cardiovascular effects beyond those seen with methylphenidate alone.

7.8 Drugs Highly Bound to Plasma Protein

In vitro drug-displacement studies were conducted with atomoxetine and other highly-bound drugs at therapeutic concentrations. Atomoxetine did not affect the binding of warfarin, acetylsalicylic acid, phenytoin, or diazepam to human albumin. Similarly, these compounds did not affect the binding of atomoxetine to human albumin.

7.9 Drugs that Affect Gastric pH

Drugs that elevate gastric pH (magnesium hydroxide/aluminum hydroxide, omeprazole) had no effect on STRATTERA bioavailability.

8 USE IN SPECIFIC POPULATIONS

8.1 Pregnancy

Pregnancy Exposure Registry

There is a pregnancy exposure registry that monitors pregnancy outcomes in women exposed to ADHD medications, including STRATTERA, during pregnancy. Healthcare providers are encouraged to register patients by calling the National Pregnancy Registry for ADHD Medications at 1-866-961-2388 or visiting https://womensmentalhealth.org/adhd-medications/.

Risk Summary

Available published studies with atomoxetine use in pregnant women are insufficient to establish a drug-associated risk of major birth defects, miscarriage or adverse maternal or fetal outcomes.

Some animal reproduction studies of atomoxetine had adverse developmental outcomes. One of 3 studies in pregnant rabbits dosed during organogenesis resulted in decreased live fetuses and an increase in early resorptions, as well as slight increases in the incidences of atypical origin of carotid artery and absent subclavian artery. These effects were observed at plasma levels (AUC) 3 times and 0.4 times the human plasma levels in extensive and poor metabolizers receiving the maximum recommended human dose (MRHD), respectively. In rats dosed prior to mating and during organogenesis a decrease in fetal weight (female only) and an increase in the incidence of incomplete ossification of the vertebral arch in fetuses were observed at a dose approximately 5 times the MRHD on a mg/m^2 basis. In one of 2 studies in which rats were dosed prior to mating through the periods of organogenesis and lactation, decreased pup weight and decreased pup survival were observed at doses corresponding to 5-6 times the MRHD on a mg/m^2 basis. No adverse fetal effects were seen in pregnant rats dosed during the organogenesis period (see Data).

The estimated background risk of major birth defects and miscarriage for the indicated population is unknown. All pregnancies have a background risk of birth defect, loss, or other adverse outcomes. In the U.S. general population, the estimated background risk of major birth defects and miscarriage in clinically recognized pregnancies is 2-4% and 15-20%, respectively.

Data

Animal Data

Pregnant rabbits were treated with up to 100 mg/kg/day of atomoxetine by gavage throughout the period of organogenesis. At this dose, in 1 of 3 studies, a decrease in live fetuses and an increase in early resorptions was observed. Slight increases in the incidences of atypical origin of carotid artery and absent subclavian artery were observed. These findings were observed at doses that caused slight maternal toxicity. The no-effect dose for these findings was 30 mg/kg/day. The 100 mg/kg dose is approximately 23 times the MRHD on a mg/m^2 basis; plasma levels (AUC) of atomoxetine at this dose in rabbits are estimated to be 3.3 times (extensive metabolizers) or 0.4 times (poor metabolizers) those in humans receiving the MRHD.

Rats were treated with up to approximately 50 mg/kg/day of atomoxetine (approximately 6 times the MRHD on a mg/m2 basis) in the diet from 2 weeks (females) or 10 weeks (males) prior to mating through the periods of organogenesis and lactation. In 1 of 2 studies, decreases in pup weight and pup survival were observed. The decreased pup survival was also seen at 25 mg/kg (but not at 13 mg/kg). In a study in which rats were treated with atomoxetine in the diet from 2 weeks (females) or 10 weeks (males) prior to mating throughout the period of organogenesis, a decrease in fetal weight (female only) and an increase in the incidence of incomplete ossification of the vertebral arch in fetuses were observed at 40 mg/kg/day (approximately 5 times the MRHD on a mg/m^2 basis) but not at 20 mg/kg/day.

No adverse fetal effects were seen when pregnant rats were treated with up to 150 mg/kg/day (approximately 17 times the MRHD on a mg/m^2 basis) by gavage throughout the period of organogenesis.

8.2 Lactation

Risk Summary

There are no data on the presence of atomoxetine or its metabolite in human milk, the effects on the breastfed child, or the effects on milk production. Atomoxetine is present in animal milk. When a drug is present in animal milk, it is likely that the drug will be present in human milk.

The developmental and health benefits of breastfeeding should be considered along with the mother’s clinical need for STRATTERA and any potential adverse effects on the breastfed child from STRATTERA or from the underlying maternal condition.

8.4 Pediatric Use

Anyone considering the use of STRATTERA in a child or adolescent must balance the potential risks with the clinical need [see Boxed Warning and Warnings and Precautions (5.1)].

The pharmacokinetics of atomoxetine in children and adolescents are similar to those in adults. The safety, efficacy, and pharmacokinetics of STRATTERA in pediatric patients less than 6 years of age have not been evaluated.

A study was conducted in young rats to evaluate the effects of atomoxetine on growth and neurobehavioral and sexual development. Rats were treated with 1, 10, or 50 mg/kg/day (approximately 0.2, 2, and 8 times, respectively, the maximum human dose on a mg/m^2 basis) of atomoxetine given by gavage from the early postnatal period (Day 10 of age) through adulthood. Slight delays in onset of vaginal patency (all doses) and preputial separation (10 and 50 mg/kg), slight decreases in epididymal weight and sperm number (10 and 50 mg/kg), and a slight decrease in corpora lutea (50 mg/kg) were seen, but there were no effects on fertility or reproductive performance. A slight delay in onset of incisor eruption was seen at 50 mg/kg. A slight increase in motor activity was seen on Day 15 (males at 10 and 50 mg/kg and females at 50 mg/kg) and on Day 30 (females at 50 mg/kg) but not on Day 60 of age. There were no effects on learning and memory tests. The significance of these findings to humans is unknown.

8.5 Geriatric Use

The safety, efficacy and pharmacokinetics of STRATTERA in geriatric patients have not been evaluated.

8.6 Hepatic Insufficiency

Atomoxetine exposure (AUC) is increased, compared with normal subjects, in EM subjects with moderate (Child-Pugh Class B) (2-fold increase) and severe (Child-Pugh Class C) (4-fold increase) hepatic insufficiency. Dosage adjustment is recommended for patients with moderate or severe hepatic insufficiency [see Dosage and Administration (2.3)].

8.7 Renal Insufficiency

EM subjects with end stage renal disease had higher systemic exposure to atomoxetine than healthy subjects (about a 65% increase), but there was no difference when exposure was corrected for mg/kg dose. STRATTERA can therefore be administered to ADHD patients with end stage renal disease or lesser degrees of renal insufficiency using the normal dosing regimen.

8.8 Gender

Gender did not influence atomoxetine disposition.

8.9 Ethnic Origin

Ethnic origin did not influence atomoxetine disposition (except that PMs are more common in Caucasians).

8.10 Patients with Concomitant Illness

Tics in patients with ADHD and comorbid Tourette's Disorder — Atomoxetine administered in a flexible dose range of 0.5 to 1.5 mg/kg/day (mean dose of 1.3 mg/kg/day) and placebo were compared in 148 randomized pediatric (age 7-17 years) subjects with a DSM-IV diagnosis of ADHD and comorbid tic disorder in an 18 week, double-blind, placebo-controlled study in which the majority (80%) enrolled in this trial with Tourette's Disorder (Tourette's Disorder: 116 subjects; chronic motor tic disorder: 29 subjects). A non-inferiority analysis revealed that STRATTERA did not worsen tics in these patients as determined by the Yale Global Tic Severity Scale Total Score (YGTSS). Out of 148 patients who entered the acute treatment phase, 103 (69.6%) patients discontinued the study. The primary reason for discontinuation in both the atomoxetine (38 of 76 patients, 50.0%) and placebo (45 of 72 patients, 62.5%) treatment groups was identified as lack of efficacy with most of the patients discontinuing at Week 12. This was the first visit where patients with a CGI-S≥4 could also meet the criteria for “clinical non-responder” (CGI-S remained the same or increased from study baseline) and be eligible to enter an open-label extension study with atomoxetine. There have been postmarketing reports of tics [see Adverse Reactions (6.2)].

Anxiety in patients with ADHD and comorbid Anxiety Disorders – In two post-marketing, double-blind, placebo-controlled trials, it has been demonstrated that treating patients with ADHD and comorbid anxiety disorders with STRATTERA does not worsen their anxiety.

In a 12-week double-blind, placebo-controlled trial, 176 patients, aged 8-17, who met DSM-IV criteria for ADHD and at least one of the anxiety disorders of separation anxiety disorder, generalized anxiety disorder or social phobia were randomized. Following a 2-week double-blind placebo lead-in, STRATTERA was initiated at 0.8 mg/kg/day with increase to a target dose of 1.2 mg/kg/day (median dose 1.30 mg/kg/day +/- 0.29 mg/kg/day). STRATTERA did not worsen anxiety in these patients as determined by the Pediatric Anxiety Rating Scale (PARS). Of the 158 patients who completed the double-blind placebo lead-in, 26 (16%) patients discontinued the study.

In a separate 16-week, double-blind, placebo-controlled trial, 442 patients aged 18-65, who met DSM-IV criteria for adult ADHD and social anxiety disorder (23% of whom also had Generalized Anxiety Disorder) were randomized. Following a 2-week double-blind placebo lead-in, STRATTERA was initiated at 40 mg/day to a maximum dose of 100 mg/day (mean daily dose 83 mg/day +/- 19.5 mg/day). STRATTERA did not worsen anxiety in these patients as determined by the Liebowitz Social Anxiety Scale (LSAS). Of the 413 patients who completed the double-blind placebo lead-in, 149 (36.1%) patients discontinued the study. There have been postmarketing reports of anxiety [see Adverse Reactions (6.2)].

9 DRUG ABUSE AND DEPENDENCE

9.1 Controlled Substance

STRATTERA is not a controlled substance.

9.2 Abuse

In a randomized, double-blind, placebo-controlled, abuse-potential study in adults comparing effects of STRATTERA and placebo, STRATTERA was not associated with a pattern of response that suggested stimulant or euphoriant properties.

9.3 Dependence

Clinical study data in over 2000 children, adolescents, and adults with ADHD and over 1200 adults with depression showed only isolated incidents of drug diversion or inappropriate self-administration associated with STRATTERA. There was no evidence of symptom rebound or adverse reactions suggesting a drug-discontinuation or withdrawal syndrome.

Animal Experience — Drug discrimination studies in rats and monkeys showed inconsistent stimulus generalization between atomoxetine and cocaine.

10 OVERDOSAGE

10.1 Human Experience

There is limited clinical trial experience with STRATTERA overdose. During postmarketing, there have been fatalities reported involving a mixed ingestion overdose of STRATTERA and at least one other drug. There have been no reports of death involving overdose of STRATTERA alone, including intentional overdoses at amounts up to 1400 mg. In some cases of overdose involving STRATTERA, seizures have been reported. The most commonly reported symptoms accompanying acute and chronic overdoses of STRATTERA were gastrointestinal symptoms, somnolence, dizziness, tremor, and abnormal behavior. Hyperactivity and agitation have also been reported. Signs and symptoms consistent with mild to moderate sympathetic nervous system activation (e.g., tachycardia, blood pressure increased, mydriasis, dry mouth) have also been observed. Most events were mild to moderate. Less commonly, there have been reports of QT prolongation and mental changes, including disorientation and hallucinations [see Clinical Pharmacology (12.2)].

10.2 Management of Overdose

Consult with a Certified Poison Control Center for up to date guidance and advice. Because atomoxetine is highly protein-bound, dialysis is not likely to be useful in the treatment of overdose.

11 DESCRIPTION

STRATTERA® (atomoxetine) is a selective norepinephrine reuptake inhibitor. Atomoxetine HCl is the R(-) isomer as determined by x-ray diffraction. The chemical designation is (-)-N-Methyl-3-phenyl-3-(o-tolyloxy)-propylamine hydrochloride. The molecular formula is C17H21NO•HCl, which corresponds to a molecular weight of 291.82. The chemical structure is:

Atomoxetine HCl is a white to practically white solid, which has a solubility of 27.8 mg/mL in water.

STRATTERA capsules are intended for oral administration only.

Each capsule contains atomoxetine HCl equivalent to 10, 18, 25, 40, 60, 80, or 100 mg of atomoxetine. The capsules also contain pregelatinized starch and dimethicone. The capsule shells contain gelatin, sodium lauryl sulfate, and other inactive ingredients. The capsule shells also contain one or more of the following:

FD&C Blue No. 2, synthetic yellow iron oxide, titanium dioxide, red iron oxide. The capsules are imprinted with edible black ink.

12 CLINICAL PHARMACOLOGY

12.1 Mechanism of Action

The precise mechanism by which atomoxetine produces its therapeutic effects in Attention-Deficit/Hyperactivity Disorder (ADHD) is unknown, but is thought to be related to selective inhibition of the pre-synaptic norepinephrine transporter, as determined in ex vivo uptake and neurotransmitter depletion studies.

12.2 Pharmacodynamics

An exposure-response analysis encompassing doses of atomoxetine (0.5, 1.2 or 1.8 mg/kg/day) or placebo demonstrated atomoxetine exposure correlates with efficacy as measured by the Attention-Deficit/Hyperactivity Disorder Rating Scale-IV-Parent Version: Investigator administered and scored. The exposure-efficacy relationship was similar to that observed between dose and efficacy with median exposures at the two highest doses resulting in near maximal changes from baseline [see Clinical Studies (14.2)].

Cardiac Electrophysiology — The effect of STRATTERA on QTc prolongation was evaluated in a randomized, double-blinded, positive-(moxifloxacin 400 mg) and placebo-controlled, cross-over study in healthy male CYP2D6 poor metabolizers. A total of 120 healthy subjects were administered STRATTERA (20 mg and 60 mg) twice daily for 7 days. No large changes in QTc interval (i.e., increases >60 msec from baseline, absolute QTc >480 msec) were observed in the study. However, small changes in QTc interval cannot be excluded from the current study, because the study failed to demonstrate assay sensitivity. There was a slight increase in QTc interval with increased atomoxetine concentration.

12.3 Pharmacokinetics

Atomoxetine is well-absorbed after oral administration and is minimally affected by food. It is eliminated primarily by oxidative metabolism through the cytochrome P450 2D6 (CYP2D6) enzymatic pathway and subsequent glucuronidation. Atomoxetine has a half-life of about 5 hours. A fraction of the population (about 7% of Caucasians and 2% of African Americans) are poor metabolizers (PMs) of CYP2D6 metabolized drugs. These individuals have reduced activity in this pathway resulting in 10-fold higher AUCs, 5-fold higher peak plasma concentrations, and slower elimination (plasma half-life of about 24 hours) of atomoxetine compared with people with normal activity [extensive metabolizers (Ems)]. Drugs that inhibit CYP2D6, such as fluoxetine, paroxetine, and quinidine, cause similar increases in exposure.

The pharmacokinetics of atomoxetine have been evaluated in more than 400 children and adolescents in selected clinical trials, primarily using population pharmacokinetic studies. Single-dose and steady-state individual pharmacokinetic data were also obtained in children, adolescents, and adults. When doses were normalized to a mg/kg basis, similar half-life, Cmax, and AUC values were observed in children, adolescents, and adults. Clearance and volume of distribution after adjustment for body weight were also similar.

Absorption and distribution — Atomoxetine is rapidly absorbed after oral administration, with absolute bioavailability of about 63% in Ems and 94% in PMs. Maximal plasma concentrations (Cmax) are reached approximately 1 to 2 hours after dosing.

STRATTERA can be administered with or without food. Administration of STRATTERA with a standard high-fat meal in adults did not affect the extent of oral absorption of atomoxetine (AUC), but did decrease the rate of absorption, resulting in a 37% lower Cmax, and delayed Tmax by 3 hours. In clinical trials with children and adolescents, administration of STRATTERA with food resulted in a 9% lower Cmax.

The steady-state volume of distribution after intravenous administration is 0.85 L/kg indicating that atomoxetine distributes primarily into total body water. Volume of distribution is similar across the patient weight range after normalizing for body weight.

At therapeutic concentrations, 98% of atomoxetine in plasma is bound to protein, primarily albumin.

Metabolism and elimination — Atomoxetine is metabolized primarily through the CYP2D6 enzymatic pathway. People with reduced activity in this pathway (PMs) have higher plasma concentrations of atomoxetine compared with people with normal activity (Ems). For PMs, AUC of atomoxetine is approximately 10-fold and Css, max is about 5-fold greater than Ems. Laboratory tests are available to identify CYP2D6 PMs. Coadministration of STRATTERA with potent inhibitors of CYP2D6, such as fluoxetine, paroxetine, or quinidine, results in a substantial increase in atomoxetine plasma exposure, and dosing adjustment may be necessary [see Warnings and Precautions (5.13)]. Atomoxetine did not inhibit or induce the CYP2D6 pathway.

The major oxidative metabolite formed, regardless of CYP2D6 status, is 4-hydroxyatomoxetine, which is glucuronidated. 4-Hydroxyatomoxetine is equipotent to atomoxetine as an inhibitor of the norepinephrine transporter but circulates in plasma at much lower concentrations (1% of atomoxetine concentration in Ems and 0.1% of atomoxetine concentration in PMs). 4-Hydroxyatomoxetine is primarily formed by CYP2D6, but in PMs, 4-hydroxyatomoxetine is formed at a slower rate by several other cytochrome P450 enzymes. N-Desmethylatomoxetine is formed by CYP2C19 and other cytochrome P450 enzymes, but has substantially less pharmacological activity compared with atomoxetine and circulates in plasma at lower concentrations (5% of atomoxetine concentration in Ems and 45% of atomoxetine concentration in PMs).

Mean apparent plasma clearance of atomoxetine after oral administration in adult Ems is 0.35 L/hr/kg and the mean half-life is 5.2 hours. Following oral administration of atomoxetine to PMs, mean apparent plasma clearance is 0.03 L/hr/kg and mean half-life is 21.6 hours. For PMs, AUC of atomoxetine is approximately 10-fold and Css, max is about 5-fold greater than Ems. The elimination half-life of 4-hydroxyatomoxetine is similar to that of N-desmethylatomoxetine (6 to 8 hours) in Em subjects, while the half-life of N-desmethylatomoxetine is much longer in PM subjects (34 to 40 hours).

Atomoxetine is excreted primarily as 4-hydroxyatomoxetine-O-glucuronide, mainly in the urine (greater than 80% of the dose) and to a lesser extent in the feces (less than 17% of the dose). Only a small fraction of the STRATTERA dose is excreted as unchanged atomoxetine (less than 3% of the dose), indicating extensive biotransformation.

[See Use in Specific Populations (8.4, 8.5, 8.6, 8.7, 8.8, 8.9)].

13 NONCLINICAL TOXICOLOGY

13.1 Carcinogenesis, Mutagenesis, Impairment of Fertility

Carcinogenesis — Atomoxetine HCl was not carcinogenic in rats and mice when given in the diet for 2 years at time-weighted average doses up to 47 and 458 mg/kg/day, respectively. The highest dose used in rats is approximately 8 and 5 times the maximum recommended human dose (MRHD) in children and adults, respectively, on a mg/m^2 basis. Plasma levels (AUC) of atomoxetine at this dose in rats are estimated to be 1.8 times (extensive metabolizers) or 0.2 times (poor metabolizers) those in humans receiving the maximum human dose. The highest dose used in mice is approximately 39 and 26 times the MRHD in children and adults, respectively, on a mg/m^2 basis.

Mutagenesis — Atomoxetine HCl was negative in a battery of genotoxicity studies that included a reverse point mutation assay (Ames Test), an in vitro mouse lymphoma assay, a chromosomal aberration test in Chinese hamster ovary cells, an unscheduled DNA synthesis test in rat hepatocytes, and an in vivo micronucleus test in mice. However, there was a slight increase in the percentage of Chinese hamster ovary cells with diplochromosomes, suggesting endoreduplication (numerical aberration).

The metabolite N-desmethylatomoxetine HCl was negative in the Ames Test, mouse lymphoma assay, and unscheduled DNA synthesis test.

Impairment of fertility — Atomoxetine HCl did not impair fertility in rats when given in the diet at doses of up to 57 mg/kg/day, which is approximately 6 times the MRHD on a mg/m^2 basis.

14 CLINICAL STUDIES

14.1 ADHD Studies in Children and Adolescents

Acute Studies — The effectiveness of STRATTERA in the treatment of ADHD was established in 4 randomized, double-blind, placebo-controlled studies of pediatric patients (ages 6 to 18). Approximately one-third of the patients met DSM-IV criteria for inattentive subtype and two-thirds met criteria for both inattentive and hyperactive/impulsive subtypes.

Signs and symptoms of ADHD were evaluated by a comparison of mean change from baseline to endpoint for STRATTERA- and placebo-treated patients using an intent-to-treat analysis of the primary outcome measure, the investigator administered and scored ADHD Rating Scale-IV-Parent Version (ADHDRS) total score including hyperactive/impulsive and inattentive subscales. Each item on the ADHDRS maps directly to one symptom criterion for ADHD in the DSM-IV.

In Study 1, an 8-week randomized, double-blind, placebo-controlled, dose-response, acute treatment study of children and adolescents aged 8 to 18 (N=297), patients received either a fixed dose of STRATTERA (0.5, 1.2, or 1.8 mg/kg/day) or placebo. STRATTERA was administered as a divided dose in the early morning and late afternoon/early evening. At the 2 higher doses, improvements in ADHD symptoms were statistically significantly superior in STRATTERA-treated patients compared with placebo-treated patients as measured on the ADHDRS scale. The 1.8 mg/kg/day STRATTERA dose did not provide any additional benefit over that observed with the 1.2 mg/kg/day dose. The 0.5 mg/kg/day STRATTERA dose was not superior to placebo.

In Study 2, a 6-week randomized, double-blind, placebo-controlled, acute treatment study of children and adolescents aged 6 to 16 (N=171), patients received either STRATTERA or placebo. STRATTERA was administered as a single dose in the early morning and titrated on a weight-adjusted basis according to clinical response, up to a maximum dose of 1.5 mg/kg/day. The mean final dose of STRATTERA was approximately 1.3 mg/kg/day. ADHD symptoms were statistically significantly improved on STRATTERA compared with placebo, as measured on the ADHDRS scale. This study shows that STRATTERA is effective when administered once daily in the morning.

In 2 identical, 9-week, acute, randomized, double-blind, placebo-controlled studies of children aged 7 to 13 (Study 3, N=147; Study 4, N=144), STRATTERA and methylphenidate were compared with placebo. STRATTERA was administered as a divided dose in the early morning and late afternoon (after school) and titrated on a weight-adjusted basis according to clinical response. The maximum recommended STRATTERA dose was 2.0 mg/kg/day. The mean final dose of STRATTERA for both studies was approximately 1.6 mg/kg/day. In both studies, ADHD symptoms statistically significantly improved more on STRATTERA than on placebo, as measured on the ADHDRS scale.

Examination of population subsets based on gender and age (<12 and 12 to 17) did not reveal any differential responsiveness on the basis of these subgroupings. There was not sufficient exposure of ethnic groups other than Caucasian to allow exploration of differences in these subgroups.

Maintenance Study — The effectiveness of STRATTERA in the maintenance treatment of ADHD was established in an outpatient study of children and adolescents (ages 6-15 years). Patients meeting DSM-IV criteria for ADHD who showed continuous response for about 4 weeks during an initial 10 week open-label treatment phase with STRATTERA (1.2 to 1.8 mg/kg/day) were randomized to continuation of their current dose of STRATTERA (N=292) or to placebo (N=124) under double-blind treatment for observation of relapse. Response during the open-label phase was defined as CGI-ADHD-S score ≤2 and a reduction of at least 25% from baseline in ADHDRS-IV-Parent:Inv total score. Patients who were assigned to STRATTERA and showed continuous response for approximately 8 months during the first double-blind treatment phase were again randomized to continuation of their current dose of STRATTERA (N=81) or to placebo (N=82) under double-blind treatment for observation of relapse. Relapse during the double-blind phase was defined as CGI-ADHD-S score increases of at least 2 from the end of open-label phase and ADHDRS-IV-Parent:Inv total score returns to ≥90% of study entry score for 2 consecutive visits. In both double-blind phases, patients receiving continued STRATTERA treatment experienced significantly longer times to relapse than those receiving placebo.

14.2 ADHD Studies in Adults

The effectiveness of STRATTERA in the treatment of ADHD was established in 2 randomized, double-blind, placebo-controlled clinical studies of adult patients, age 18 and older, who met DSM-IV criteria for ADHD.

Signs and symptoms of ADHD were evaluated using the investigator-administered Conners Adult ADHD Rating Scale Screening Version (CAARS), a 30-item scale. The primary effectiveness measure was the 18-item Total ADHD Symptom score (the sum of the inattentive and hyperactivity/impulsivity subscales from the CAARS) evaluated by a comparison of mean change from baseline to endpoint using an intent-to-treat analysis.

In 2 identical, 10-week, randomized, double-blind, placebo-controlled acute treatment studies (Study 5, N=280; Study 6, N=256), patients received either STRATTERA or placebo. STRATTERA was administered as a divided dose in the early morning and late afternoon/early evening and titrated according to clinical response in a range of 60 to 120 mg/day. The mean final dose of STRATTERA for both studies was approximately 95 mg/day. In both studies, ADHD symptoms were statistically significantly improved on STRATTERA, as measured on the ADHD Symptom score from the CAARS scale.

Examination of population subsets based on gender and age (<42 and ≥42) did not reveal any differential responsiveness on the basis of these subgroupings. There was not sufficient exposure of ethnic groups other than Caucasian to allow exploration of differences in these subgroups.

16 HOW SUPPLIED/STORAGE AND HANDLING

16.1 How Supplied

STRATTERA® Capsules | 10 mga | 18 mga | 25 mga | 40 mga | 60 mga | 80 mga | 100 mga
Color | Opaque White, Opaque White | Gold, Opaque White | Opaque Blue, Opaque White | Opaque Blue, Opaque Blue | Opaque Blue, Gold | Opaque Brown, Opaque White | Opaque Brown, Opaque Brown
Identification | LILLY 3227 | LILLY 3238 | LILLY 3228 | LILLY 3229 | LILLY 3239 | LILLY 3250 | LILLY 3251
 | 10 mg | 18 mg | 25 mg | 40 mg | 60 mg | 80 mg | 100 mg
NDC Codes:
Bottles of 30 | 0002-3227-30 | 0002-3238-30 | 0002-3228-30 | 0002-3229-30 | 0002-3239-30 | 0002-3250-30 | 0002-3251-30
a Atomoxetine base equivalent.

16.2 Storage and Handling

Store at 25°C (77°F); excursions permitted to 15° to 30°C (59° to 86°F) [see USP Controlled Room Temperature].

17 PATIENT COUNSELING INFORMATION

Advise the patient to read the FDA-approved patient labeling (Medication Guide).

Suicide Risk

Patients, their families, and their caregivers should be encouraged to be alert to the emergence of anxiety, agitation, panic attacks, insomnia, irritability, hostility, aggressiveness, impulsivity, akathisia (psychomotor restlessness), hypomania, mania, other unusual changes in behavior, depression, and suicidal ideation, especially early during STRATTERA treatment and when the dose is adjusted. Families and caregivers of patients should be advised to observe for the emergence of such symptoms on a day-to-day basis, since changes may be abrupt. Such symptoms should be reported to the patient's prescriber or health professional, especially if they are severe, abrupt in onset, or were not part of the patient's presenting symptoms. Symptoms such as these may be associated with an increased risk for suicidal thinking and behavior and indicate a need for very close monitoring and possibly changes in the medication [see Warnings and Precautions (5.1)].

Severe Liver Injury

Patients initiating STRATTERA should be cautioned that severe liver injury may develop. Patients should be instructed to contact their healthcare provider immediately should they develop pruritus, dark urine, jaundice, right upper quadrant tenderness, or unexplained “flu-like” symptoms [see Warnings and Precautions (5.2)].

Screening Patients for Bipolar Disorder

Instruct patients and their caregivers to look for signs of activation of mania/hypomania [see Warnings and Precautions (5.6)].

Aggression or Hostility

Instruct patients and their caregivers to contact their healthcare provider as soon as possible should they notice an increase in aggression or hostility [see Warnings and Precautions (5.7)].

Priapism

Rare postmarketing cases of priapism, defined as painful and nonpainful penile erection lasting more than 4 hours, have been reported for pediatric and adult patients treated with STRATTERA. The parents or guardians of pediatric patients taking STRATTERA and adult patients taking STRATTERA should be instructed that priapism requires prompt medical attention [see Warnings and Precautions (5.10)].

Ocular Irritant

STRATTERA is an ocular irritant. STRATTERA capsules are not intended to be opened. In the event of capsule content coming in contact with the eye, the affected eye should be flushed immediately with water, and medical advice obtained. Hands and any potentially contaminated surfaces should be washed as soon as possible.

Drug-Drug Interaction

Patients should be instructed to consult a healthcare provider if they are taking or plan to take any prescription or over-the-counter medicines, dietary supplements, or herbal remedies.

Pregnancy Registry

Advise patients that there is a pregnancy registry that monitors pregnancy outcomes in women exposed to atomoxetine during pregnancy [see Use in Specific Populations (8.1)].

Food

Patients may take STRATTERA with or without food.

Missed Dose

If patients miss a dose, they should be instructed to take it as soon as possible, but should not take more than the prescribed total daily amount of STRATTERA in any 24-hour period.

Interference with Psychomotor Performance

Patients should be instructed to use caution when driving a car or operating hazardous machinery until they are reasonably certain that their performance is not affected by atomoxetine.

Marketed by: Lilly USA, LLC
Indianapolis, IN 46285, USA

Copyright © 2002, 2022, Eli Lilly and Company. All rights reserved.

STR-0005-USPI-20220106

MEDICATION GUIDE
STRATTERA® (Stra-TAIR-a)
(atomoxetine) Capsules

Read the Medication Guide that comes with STRATTERA® before you or your child starts taking it and each time you get a refill. There may be new information. This Medication Guide does not take the place of talking to your doctor about your treatment or your child's treatment with STRATTERA.

What is the most important information I should know about STRATTERA?

The following have been reported with use of STRATTERA:

1. Suicidal thoughts and actions in children and teenagers:

Children and teenagers sometimes think about suicide, and many report trying to kill themselves. Results from STRATTERA clinical studies with over 2200 child or teenage ADHD patients suggest that some children and teenagers may have a higher chance of having suicidal thoughts or actions. Although no suicides occurred in these studies, 4 out of every 1000 patients developed suicidal thoughts. Tell your child or teenager's doctor if your child or teenager (or there is a family history of):

- has bipolar illness (manic-depressive illness)
- had suicide thoughts or actions before starting STRATTERA

The chance for suicidal thoughts and actions may be higher:

- early during STRATTERA treatment
- during dose adjustments

Prevent suicidal thoughts and action in your child or teenager by:

- paying close attention to your child or teenager's moods, behaviors, thoughts, and feelings during STRATTERA treatment
- keeping all follow-up visits with your child or teenager's doctor as scheduled

Watch for the following signs in your child or teenager during STRATTERA treatment:

- anxiety
- agitation
- panic attacks
- trouble sleeping
- irritability
- hostility
- aggressiveness
- impulsivity
- restlessness
- mania
- depression
- suicide thoughts

Call your child or teenager's doctor right away if they have any of the above signs, especially if they are new, sudden, or severe. Your child or teenager may need to be closely watched for suicidal thoughts and actions or need a change in medicine.

2. Severe liver damage:

STRATTERA can cause liver injury in some patients. Call your doctor right away if you or your child has the following signs of liver problems:

- itching
- right upper belly pain
- dark urine
- yellow skin or eyes
- unexplained flu-like symptoms

3. Heart-related problems:

- sudden death in patients who have heart problems or heart defects
- stroke and heart attack in adults
- increased blood pressure and heart rate

Tell your doctor if you or your child has any heart problems, heart defects, high blood pressure, or a family history of these problems. Your doctor should check you or your child carefully for heart problems before starting STRATTERA.

Your doctor should check your blood pressure or your child's blood pressure and heart rate regularly during treatment with STRATTERA.

Call your doctor right away if you or your child has any signs of heart problems such as chest pain, shortness of breath, or fainting while taking STRATTERA.

4. New mental (psychiatric) problems in children and teenagers:

- new psychotic symptoms (such as hearing voices, believing things that are not true, being suspicious) or new manic symptoms

Call your child or teenager's doctor right away about any new mental symptoms because adjusting or stopping STRATTERA treatment may need to be considered.

What Is STRATTERA?

STRATTERA is a selective norepinephrine reuptake inhibitor medicine. It is used for the treatment of attention deficit and hyperactivity disorder (ADHD). STRATTERA may help increase attention and decrease impulsiveness and hyperactivity in patients with ADHD.

STRATTERA should be used as a part of a total treatment program for ADHD that may include counseling or other therapies.

STRATTERA has not been studied in children less than 6 years old.

Who should not take STRATTERA?

STRATTERA should not be taken if you or your child:

- are taking or have taken within the past 14 days an anti-depression medicine called a monoamine oxidase inhibitor or MAOI. Some names of MAOI medicines are Nardil® (phenelzine sulfate), Parnate® (tranylcypromine sulfate) and Emsam® (selegiline transdermal system).
- have an eye problem called narrow angle glaucoma
- are allergic to anything in STRATTERA. See the end of this Medication Guide for a complete list of ingredients.
- have or have had a rare tumor called pheochromocytoma.

STRATTERA may not be right for you or your child. Before starting STRATTERA tell your doctor or your child's doctor about all health conditions (or a family history of) including:

- have or had suicide thoughts or actions
- heart problems, heart defects, irregular heart beat, high blood pressure, or low blood pressure
- mental problems, psychosis, mania, bipolar illness, or depression
- liver problems
- are pregnant or plan to become pregnant. It is not known if STRATTERA will harm your unborn baby. Talk to your doctor if you are pregnant or plan to become pregnant.
  - There is a pregnancy registry for females who are exposed to ADHD medications, including STRATTERA, during pregnancy. The purpose of the registry is to collect information about the health of females exposed to STRATTERA and their baby. If you or your child becomes pregnant during treatment with STRATTERA, talk to your healthcare provider about registering with the National Pregnancy Registry of ADHD Medications at 1-866-961-2388 or visit online at https://womensmentalhealth.org/adhdmedications/.
- are breastfeeding or plan to breastfeed. It is not known if STRATTERA passes into your breast milk. Talk to your doctor about the best way to feed your baby if you take STRATTERA.

Can STRATTERA be taken with other medicines?

Tell your doctor about all the medicines that you or your child takes including prescription and nonprescription medicines, vitamins, and herbal supplements. STRATTERA and some medicines may interact with each other and cause serious side effects. Your doctor will decide whether STRATTERA can be taken with other medicines.

Especially tell your doctor if you or your child takes:

- asthma medicines
- anti-depression medicines including MAOIs
- blood pressure medicines
- cold or allergy medicines that contain decongestants

Know the medicines that you or your child takes. Keep a list of your medicines with you to show your doctor and pharmacist.

Do not start any new medicine while taking STRATTERA without talking to your doctor first.

How should STRATTERA be taken?

- Take STRATTERA exactly as prescribed. STRATTERA comes in different dose strength capsules. Your doctor may adjust the dose until it is right for you or your child.
- Do not chew, crush, or open the capsules. Swallow STRATTERA capsules whole with water or other liquids. Tell your doctor if you or your child cannot swallow STRATTERA whole. A different medicine may need to be prescribed.
- Avoid touching a broken STRATTERA capsule. Wash hands and surfaces that touched an open STRATTERA capsule. If any of the powder gets in your eyes or your child's eyes, rinse them with water right away and call your doctor.
- STRATTERA can be taken with or without food.
- STRATTERA is usually taken once or twice a day. Take STRATTERA at the same time each day to help you remember. If you miss a dose of STRATTERA, take it as soon as you remember that day. If you miss a day of STRATTERA, do not double your dose the next day. Just skip the day you missed.
- From time to time, your doctor may stop STRATTERA treatment for a while to check ADHD symptoms.
- Your doctor may do regular checks of the blood, heart, and blood pressure while taking STRATTERA. Children should have their height and weight checked often while taking STRATTERA. STRATTERA treatment may be stopped if a problem is found during these check-ups.
- If you or your child takes too much STRATTERA or overdoses, call your doctor or poison control center right away, or get emergency treatment.

What are possible side effects of STRATTERA?

See “What is the most important information I should know about STRATTERA?” for information on reported suicidal thoughts and actions, other mental problems, severe liver damage, and heart problems.

Other serious side effects include:

- serious allergic reactions (call your doctor if you have trouble breathing, see swelling or hives, or experience other allergic reactions)
- slowing of growth (height and weight) in children
- problems passing urine including
  - trouble starting or keeping a urine stream
  - cannot fully empty the bladder

Common side effects in children and teenagers include:

- upset stomach
- decreased appetite
- nausea or vomiting
- dizziness
- tiredness
- mood swings

Common side effects in adults include:

- constipation
- dry mouth
- nausea
- decreased appetite
- dizziness
- sexual side effects
- problems passing urine

Other information for children, teenagers, and adults:

- Erections that won't go away (priapism) have occurred rarely during treatment with STRATTERA. If you have an erection that lasts more than 4 hours, seek medical help right away. Because of the potential for lasting damage, including the potential inability to have erections, priapism should be evaluated by a doctor immediately.
- STRATTERA may affect your ability or your child's ability to drive or operate heavy machinery. Be careful until you know how STRATTERA affects you or your child.
- Talk to your doctor if you or your child has side effects that are bothersome or do not go away.

This is not a complete list of possible side effects. Call your doctor for medical advice about side effects. You may report side effects to FDA at 1-800-FDA-1088.

How should I store STRATTERA?

- Store STRATTERA in a safe place at room temperature, 59 to 86°F (15 to 30°C).
- Keep STRATTERA and all medicines out of the reach of children.

General information about STRATTERA

Medicines are sometimes prescribed for purposes other than those listed in a Medication Guide. Do not use STRATTERA for a condition for which it was not prescribed. Do not give STRATTERA to other people, even if they have the same condition. It may harm them.

This Medication Guide summarizes the most important information about STRATTERA. If you would like more information, talk with your doctor. You can ask your doctor or pharmacist for information about STRATTERA that was written for healthcare professionals. For more information about STRATTERA call 1-800-Lilly-Rx (1-800-545-5979) or visit www.strattera.com.

What are the ingredients in STRATTERA?

Active ingredient: atomoxetine hydrochloride.

Inactive ingredients: pregelatinized starch, dimethicone, gelatin, sodium lauryl sulfate, FD&C Blue No. 2, synthetic yellow iron oxide, titanium dioxide, red iron oxide, and edible black ink.

Nardil® is a registered trademark of Pfizer Inc.

Parnate® is a registered trademark of GlaxoSmithKline.

Emsam® is a registered trademark of Somerset Pharmaceuticals Inc.

This Medication Guide has been approved by the US Food and Drug Administration.

Revised: 2/2020

Marketed by: Lilly USA, LLC
Indianapolis, IN 46285, USA

Copyright © 2003, 2020, Eli Lilly and Company. All rights reserved.

STR-0001-MG-20200225

PACKAGE LABEL - STRATTERA 10 mg bottle of 30

30 Capsules

NDC 0002-3227-30

PU 3227

strattera®

atomoxetine capsules

Rx only

10 mg

Each capsule equivalent to 10 mg atomoxetine

Do not use if Lilly inner seal is missing or broken.

www.strattera.com

Lilly

PACKAGE LABEL - STRATTERA 18 mg bottle of 30

30 Capsules

NDC 0002-3238-30

PU 3238

strattera®

atomoxetine capsules

Rx only

18 mg

Each capsule equivalent to 18 mg atomoxetine

Do not use if Lilly inner seal is missing or broken.

www.strattera.com

Lilly

PACKAGE LABEL - STRATTERA 25 mg bottle of 30

30 Capsules

NDC 0002-3228-30

PU 3228

strattera®

atomoxetine capsules

Rx only

25 mg

Each capsule equivalent to 25 mg atomoxetine

Do not use if Lilly inner seal is missing or broken.

www.strattera.com

Lilly

PACKAGE LABEL - STRATTERA 40 mg bottle of 30

30 Capsules

NDC 0002-3229-30

PU 3229

strattera®

atomoxetine capsules

Rx only

40 mg

Each capsule equivalent to 40 mg atomoxetine

Do not use if Lilly inner seal is missing or broken.

www.strattera.com

Lilly

PACKAGE LABEL - STRATTERA 60 mg bottle of 30

30 Capsules

NDC 0002-3239-30

PU 3239

strattera®

atomoxetine capsules

Rx only

60 mg

Each capsule equivalent to 60 mg atomoxetine

Do not use if Lilly inner seal is missing or broken.

www.strattera.com

Lilly

PACKAGE LABEL - STRATTERA 80 mg bottle of 30

30 Capsules

NDC 0002-3250-30

PU 3250

strattera®

atomoxetine capsules

Rx only

80 mg

Each capsule equivalent to 80 mg atomoxetine

Do not use if Lilly inner seal is missing or broken.

www.strattera.com

Lilly

PACKAGE LABEL - STRATTERA 100 mg bottle of 30

30 Capsules

NDC 0002-3251-30

PU 3251

strattera®

atomoxetine capsules

Rx only

100 mg

Each capsule equivalent to 100 mg atomoxetine

Do not use if Lilly inner seal is missing or broken.

www.strattera.com

Lilly